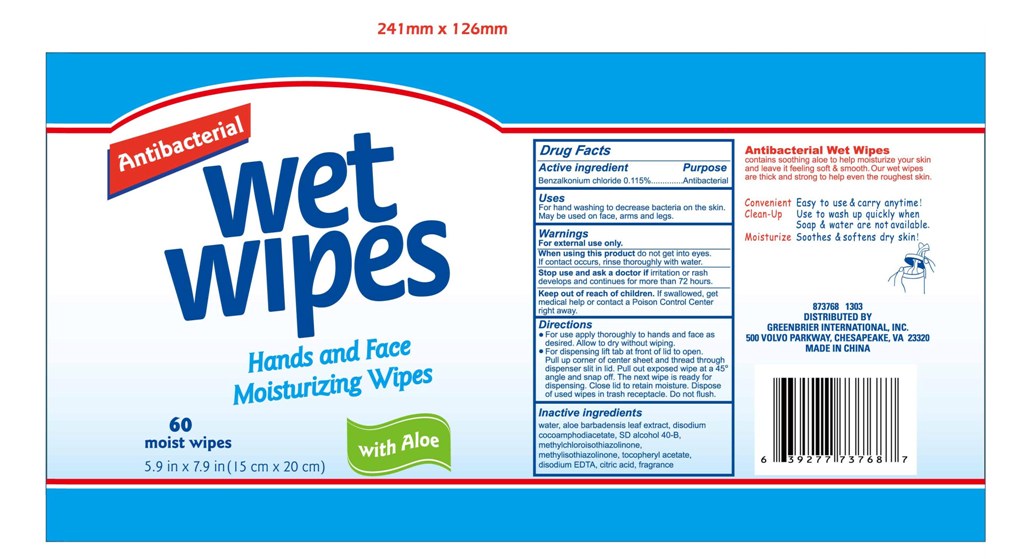 DRUG LABEL: Antibacterial Wet Wipes
NDC: 42255-586 | Form: SWAB
Manufacturer: ZHEJIANG GREENFACE HOUSEWARES CO., LTD.
Category: otc | Type: HUMAN OTC DRUG LABEL
Date: 20180108

ACTIVE INGREDIENTS: BENZALKONIUM CHLORIDE 0.115 g/100 g
INACTIVE INGREDIENTS: WATER; DISODIUM COCOAMPHODIACETATE; ALCOHOL; METHYLCHLOROISOTHIAZOLINONE; METHYLISOTHIAZOLINONE; .ALPHA.-TOCOPHEROL ACETATE; DISODIUM EDTA-COPPER; CITRIC ACID ACETATE; ALOE VERA LEAF

ANTIBACTERIAL WET WIPES 586

Active ingredient

Benzalkonium chloride 0.115%

Purpose

Antibacterial

Use

For hand washing to decrease bacteria on the skin.

May be used on face, arms and legs.

Warnings

For external use only.

When using this product do not get into eyes.

If contact occurs, rinse thoroughly with water.

Stop use and ask a doctor if irritation or rash

develops and continues for more than 72 hours.

Keep out of reach of children. If swallowed, get

medical help or contact aPoisonControlCenter

right away.

Directions

For use apply thoroughly to hands and face as

desired. Allow to dry without wiping.

For dispensing lift tab at front of lid to open.

Pull up corner of center sheet and thread through

dispenser slit in lid. Pull out exposed wipe at a 45°

angle and snap off. The next wipe is ready for

dispensing. Close lid to retain moisture. Dispose

of used wipes in trash receptacle. Do not flush.

INACTIVE INGREDIENT

water, aloe barbadensis leaf extract, disodium

cocoamphodiacetate, SD alcohol 40-B,

methylchloroisothiazolinone,

methylisothiazolinone, tocopheryl acetate,

disodium EDTA, citric acid, fragrance